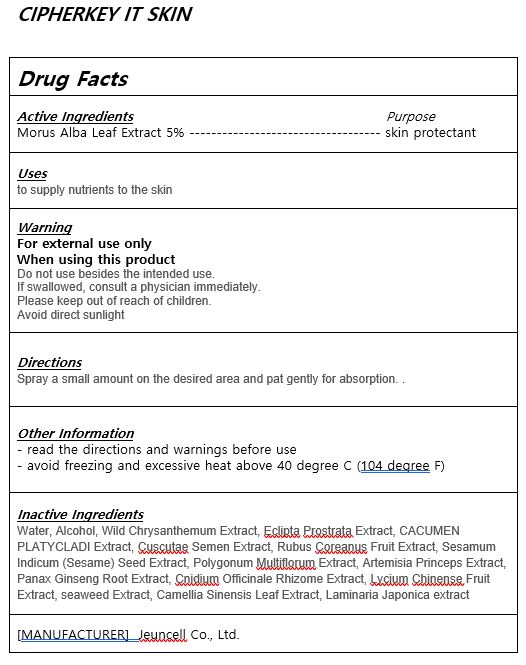 DRUG LABEL: CIPHERKEY IT SKIN
NDC: 54296-0003 | Form: LIQUID
Manufacturer: Jeuncell Co.,Ltd
Category: otc | Type: HUMAN OTC DRUG LABEL
Date: 20230922

ACTIVE INGREDIENTS: MORUS ALBA LEAF 6 g/100 mL
INACTIVE INGREDIENTS: WATER; ALCOHOL

ACTIVE INGREDIENT

Morus Alba Leaf Extract

INACTIVE INGREDIENT

Water, Alcohol, Wild Chrysanthemum Extract, Eclipta Prostrata Extract, CACUMEN PLATYCLADI Extract, Cuscutae Semen Extract,
Rubus Coreanus Fruit Extract, Sesamum Indicum (Sesame) Seed Extract, Polygonum Multiflorum Extract, Artemisia Princeps Extract,
Panax Ginseng Root Extract, Cnidium Officinale Rhizome Extract, Lycium Chinense Fruit Extract, seaweed Extract, Camellia Sinensis Leaf Extract, Laminaria Japonica extract

PURPOSE

to supply nutrients to the skin

Do not use besides the intended use.
If swallowed, consult a physician immediately.
Please keep out of reach of children.
Avoid direct sunlight

Please keep out of reach of children.

INDICATIONS AND USAGE

Spray a small amount on the desired area and pat gently for absorption.

DOSAGE AND ADMINISTRATION

for external use only